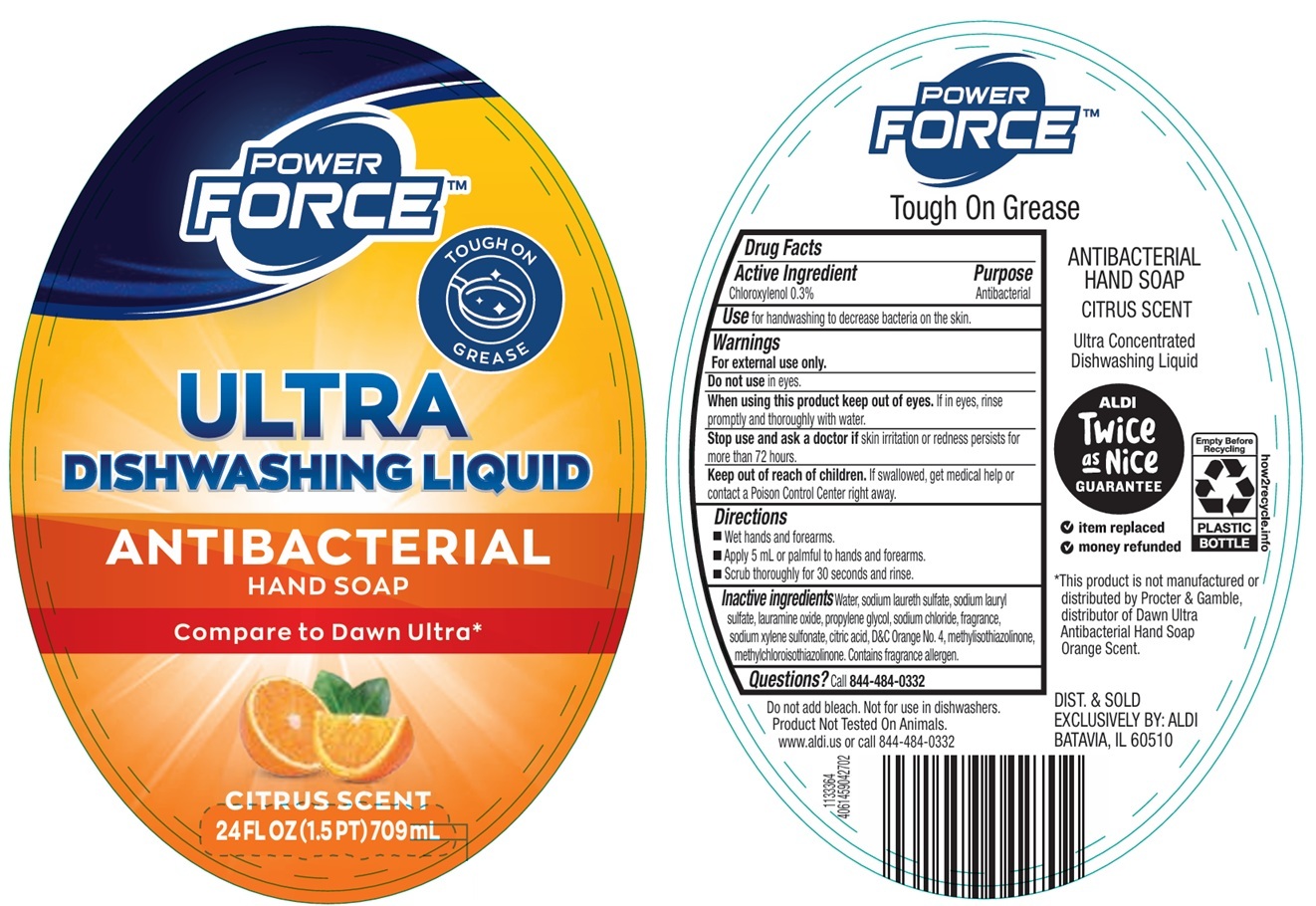 DRUG LABEL: POWER FORCE ANTIBACTERIAL HANDSOAP CITRUS SCENT
NDC: 73487-009 | Form: LIQUID
Manufacturer: KOREX CHICAGO LLC
Category: otc | Type: HUMAN OTC DRUG LABEL
Date: 20251215

ACTIVE INGREDIENTS: CHLOROXYLENOL 0.3 g/100 mL
INACTIVE INGREDIENTS: WATER; SODIUM LAURETH-3 SULFATE; SODIUM LAURYL SULFATE; LAURAMINE OXIDE; PROPYLENE GLYCOL; SODIUM CHLORIDE; SODIUM XYLENESULFONATE; CITRIC ACID MONOHYDRATE; D&C ORANGE NO. 4; METHYLISOTHIAZOLINONE; METHYLCHLOROISOTHIAZOLINONE

POWER FORCE™ ANTIBACTERIAL HAND SOAP CITRUS SCENT

Active Ingredient

Chloroxylenol 0.3%

Purpose

Antibacterial

Use

for handwashing to decrease bacteria on the skin.

Warnings

For external use only.

Do not use in eyes.

When using this product keep out of eyes. If in eyes, rinse promptly and thoroughly with water.

Stop use and ask a doctor if skin irritation or redness persists for more than 72 hours.

Keep out of reach of children. If swallowed, get medical help or contact a Poison Control Center right away.

Directions

• Wet hands and forearms.
• Apply 5 mL or palmful to hands and forearms.
• Scrub thoroughly for 30 seconds and rinse.

Inactive ingredients

Water, sodium laureth sulfate, sodium lauryl sulfate, lauramine oxide, propylene glycol, sodium chloride, fragrance, sodium xylene sulfonate, citric acid, D&C Orange No. 4, methylisothiazolinone, methylchloroisothiazolinone. Contains fragrance allergen.

Questions?

Call 844-484-0332

TOUGH ON GREASE

ULTRA DISHWASHING LIQUID

Compare to Dawn Ultra*

Do not add bleach. Not for use in dishwashers.
Product Not Tested On Animals.
www.aldi.us

Ultra Concentrated

*This product is not manufactured or distributed by Procter & Gamble, distributor of Dawn Ultra Antibacterial Hand Soap

DIST. & SOLD
EXCLUSIVELY BY: ALDI
BATAVIA, IL 60510